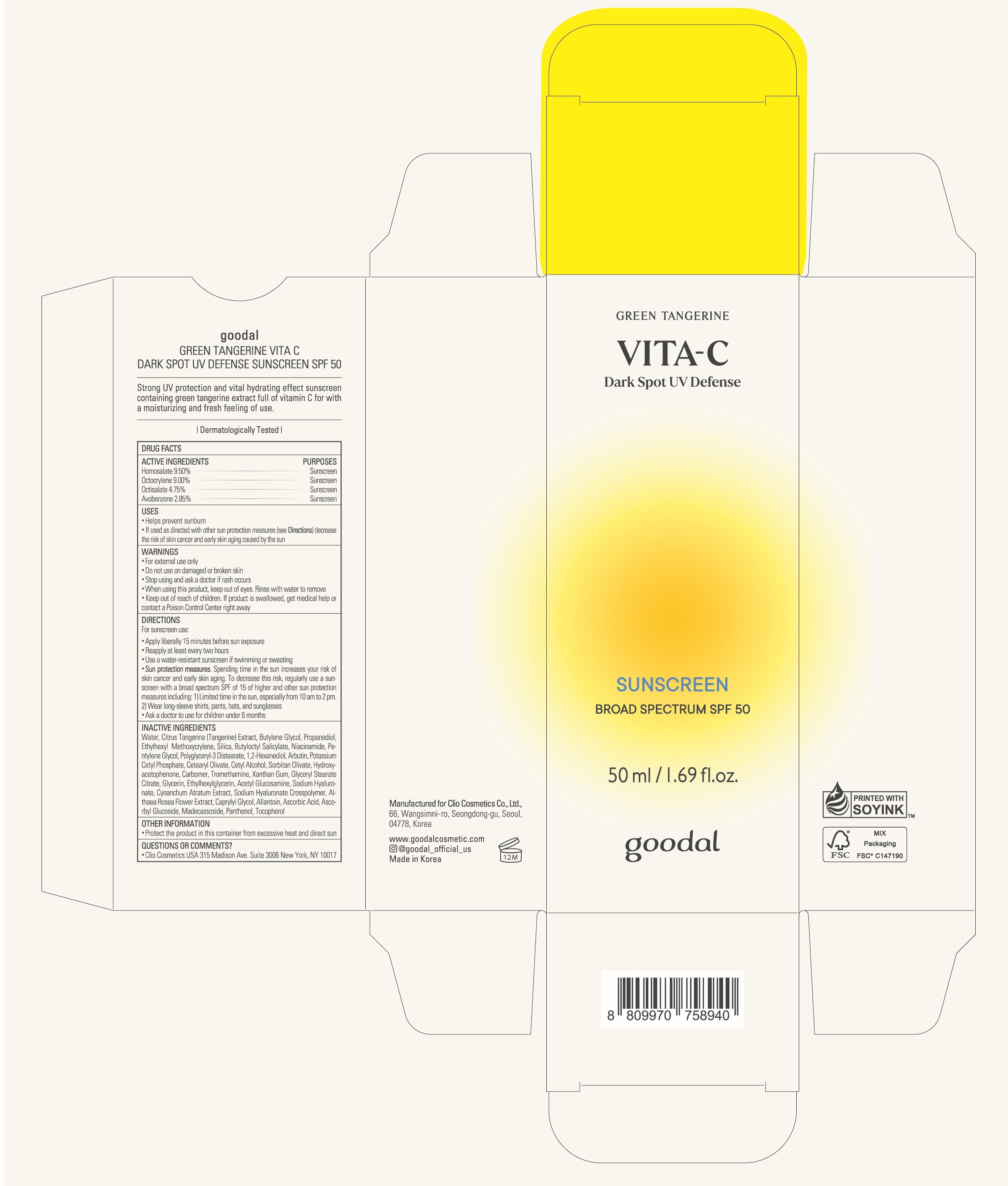 DRUG LABEL: goodal GREEN TANGERINE VITA C DARK SPOT UV DEFENSE SUNSCREEN SPF50
NDC: 84532-001 | Form: CREAM
Manufacturer: CLIO COSMETICS Co., Ltd.
Category: otc | Type: HUMAN OTC DRUG LABEL
Date: 20250416

ACTIVE INGREDIENTS: HOMOSALATE 95 mg/1 mL; OCTISALATE 47.5 mg/1 mL; OCTOCRYLENE 90 mg/1 mL; AVOBENZONE 28.5 mg/1 mL
INACTIVE INGREDIENTS: WATER; TANGERINE; BUTYLENE GLYCOL; PROPANEDIOL; ETHYLHEXYL METHOXYCRYLENE; SILICON DIOXIDE; BUTYLOCTYL SALICYLATE; NIACINAMIDE; PENTYLENE GLYCOL; POLYGLYCERYL-3 DISTEARATE; 1,2-HEXANEDIOL; ARBUTIN; POTASSIUM CETYL PHOSPHATE; CETEARYL OLIVATE; CETYL ALCOHOL; SORBITAN OLIVATE; HYDROXYACETOPHENONE; CARBOMER HOMOPOLYMER, UNSPECIFIED TYPE; TROMETHAMINE; XANTHAN GUM; GLYCERYL STEARATE CITRATE; GLYCERIN; ETHYLHEXYLGLYCERIN; N-ACETYLGLUCOSAMINE; HYALURONATE SODIUM; VINCETOXICUM ATRATUM ROOT; ALCEA ROSEA FLOWER; CAPRYLYL GLYCOL; ALLANTOIN; ASCORBIC ACID; ASCORBYL GLUCOSIDE; MADECASSOSIDE; PANTHENOL; TOCOPHEROL

84532-001_goodal GREEN TANGERINE VITA C DARK SPOT UV DEFENSE SUNSCREEN SPF50

ACTIVE INGREDIENT

Homosalate 9.50%

Octocrylene 9.00%

Octisalate 4.75%

Avobenzone 2.85%

PURPOSE

Sunscreen

INDICATIONS AND USAGE

Helps prevent sunburn
If used as directed with other sun protection measures (see Directions) decrease the risk of skin cancer and early skin aging caused by the sun

DOSAGE AND ADMINISTRATION

Apply liberally 15 minutes before sun exposure
Reapply at least every two hours
Use a water-resistant sunscreen if swimming or sweating

Sun protection measures. Spending time in the sun increases your risk of skin cancer and early skin aging. To decrease this risk, regularly use a sunscreen with a broad spectrum SPF value of 15 or higher and other sun protection measures including: 1) Limit time in the sun, especially from 10 a.m. to 2 p.m. 2) Wear long-sleeved shirts, pants, hats, and sunglasses

WARNINGS

For external use only.

Do not use on damaged or broken skin.

Stop use and ask a doctor if rash occurs.

When using this product keep out of eyes. Rinse with water to remove.

Keep out of reach of children. If swallowed, get medical help or contact a Poison Control Center right away

INACTIVE INGREDIENT

Water, Citrus Tangerina (Tangerine) Extract, Butylene Glycol, Propanediol, Ethylhexyl Methoxycrylene, Silica, Butyloctyl Salicylate, Niacinamide, Pentylene Glycol, Polyglyceryl-3 Distearate, 1,2-Hexanediol, Arbutin, Potassium Cetyl Phosphate, Cetearyl Olivate, Cetyl Alcohol, Sorbitan Olivate, Hydroxyacetophenone, Carbomer, Tromethamine, Xanthan Gum, Glyceryl Stearate Citrate, Glycerin, Ethylhexylglycerin, Acetyl Glucosamine, Sodium Hyaluronate, Cynanchum Atratum Extract, Sodium Hyaluronate Crosspolymer, Althaea Rosea Flower Extract, Caprylyl Glycol, Allantoin, Ascorbic Acid, Ascorbyl Glucoside, Madecassoside, Panthenol, Tocopherol

OTHER SAFETY INFORMATION

Protect the product in the container from excessive heat and direct sun.